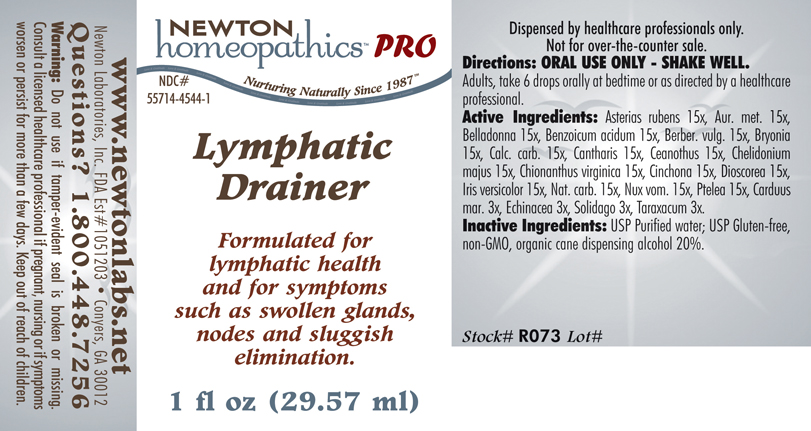 DRUG LABEL: Lymphatic Drainer 
NDC: 55714-4544 | Form: LIQUID
Manufacturer: Newton Laboratories, Inc.
Category: homeopathic | Type: HUMAN PRESCRIPTION DRUG LABEL
Date: 20110601

ACTIVE INGREDIENTS: Asterias Rubens 15 [hp_X]/1 mL; Gold 15 [hp_X]/1 mL; Atropa Belladonna 15 [hp_X]/1 mL; Benzoic Acid 15 [hp_X]/1 mL; Berberis Vulgaris Root Bark 15 [hp_X]/1 mL; Bryonia Alba Root 15 [hp_X]/1 mL; Oyster Shell Calcium Carbonate, Crude 15 [hp_X]/1 mL; Lytta Vesicatoria 15 [hp_X]/1 mL; Ceanothus Americanus Leaf 15 [hp_X]/1 mL; Chelidonium Majus 15 [hp_X]/1 mL; Cinchona Officinalis Bark 15 [hp_X]/1 mL; Chionanthus Virginicus Bark 15 [hp_X]/1 mL; Dioscorea Villosa Tuber 15 [hp_X]/1 mL; Iris Versicolor Root 15 [hp_X]/1 mL; Sodium Carbonate 15 [hp_X]/1 mL; Strychnos Nux-vomica Seed 15 [hp_X]/1 mL; Ptelea Trifoliata Bark 15 [hp_X]/1 mL; Silybum Marianum Seed 3 [hp_X]/1 mL; Echinacea, Unspecified 3 [hp_X]/1 mL; Solidago Virgaurea Flowering Top 3 [hp_X]/1 mL; Taraxacum Officinale 3 [hp_X]/1 mL
INACTIVE INGREDIENTS: Alcohol

Lymphatic Drainer

INDICATIONS & USAGE SECTION

Lymphatic Drainer Formulated for lymphatic health and for symptoms such as swollen glands, nodes and sluggish elimination.

DOSAGE & ADMINISTRATION SECTION

Directions: ORAL USE ONLY - SHAKE WELL. Adults, take 6 drops orally at bedtime or as directed by a healthcare professional.

ACTIVE INGREDIENT SECTION

Asterias rubens 15x, Aur. met. 15x, Belladonna 15x, Benzoicum acidum 15x, Berber. vulg. 15x, Bryonia 15x, Calc. carb. 15x, Cantharis 15x, Ceanothus 15x, Chelidonium majus 15x, Chionanthus virginica 15x, Cinchona 15x, Dioscorea 15x, Iris versicolor 15x, Nat. carb. 15x, Nux vom. 15x, Ptelea 15x, Carduus mar. 3x, Echinacea 3x, Solidago 3x, Taraxacum 3x.

PURPOSE SECTION

Formulated for lymphatic health and for symptoms such as swollen glands, nodes and sluggish elimination.

INACTIVE INGREDIENT SECTION

Inactive Ingredients: USP Purified Water; USP Gluten-free, non-GMO, organic cane dispensing alcohol 20%.

QUESTIONS? SECTION

www.newtonlabs.net Newton Laboratories, Inc. FDA Est # 1051203 - Conyers, GA 30012
Questions? 1.800.448.7256

WARNINGS SECTION

Warning: Do not use if tamper - evident seal is broken or missing. Consult a licensed healthcare professional if pregnant, nursing or if symptoms worsen or persist for more than a few days. Keep out of reach of children.

PREGNANCY OR BREAST FEEDING SECTION

Consult a licensed healthcare professional if pregnant, nursing or if symptoms worsen or persist for more than a few days.

KEEP OUT OF REACH OF CHILDREN SECTION

Keep out of reach of children.